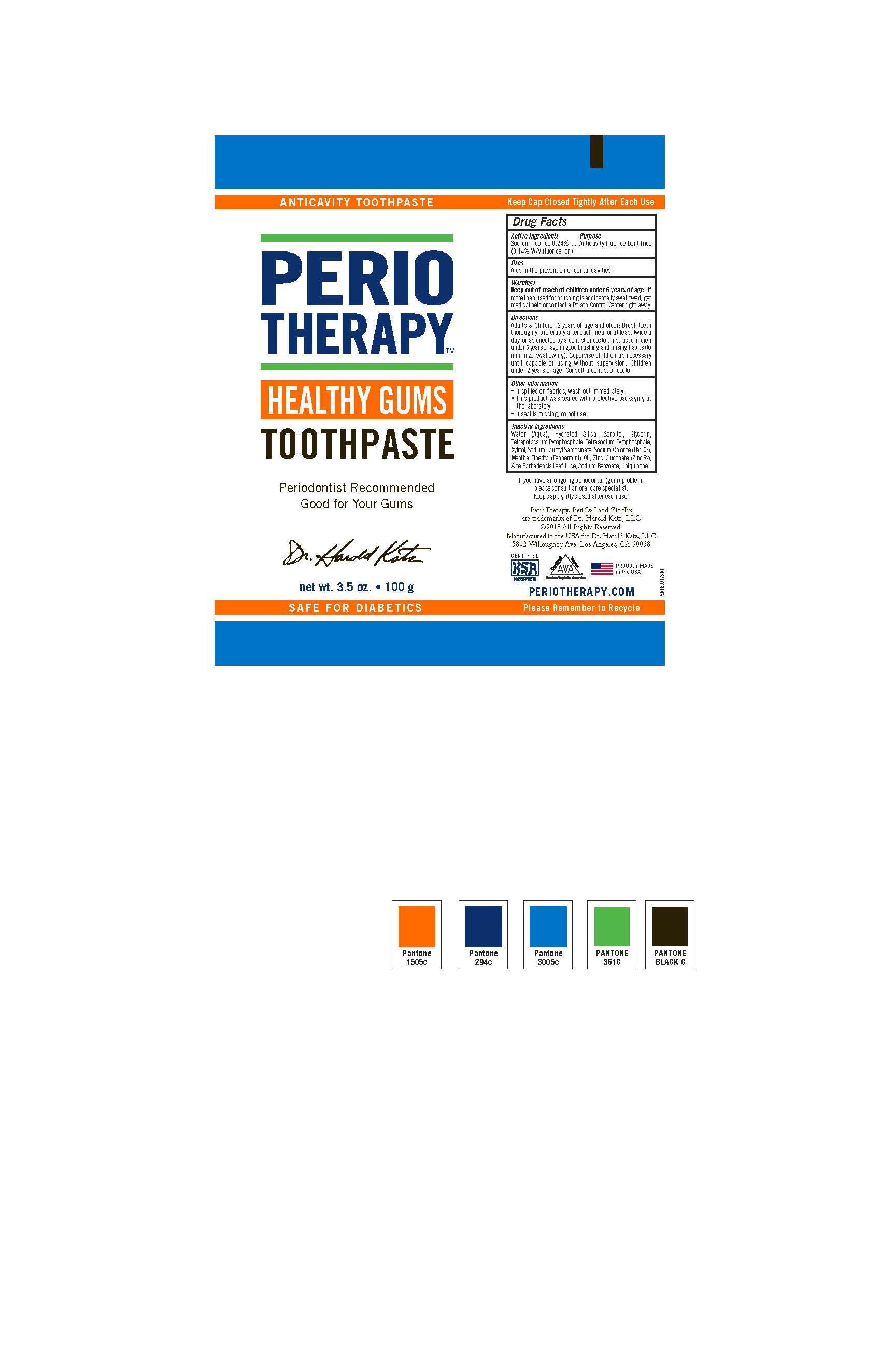 DRUG LABEL: PerioTherapy Healthy Gums
NDC: 72551-253 | Form: PASTE, DENTIFRICE
Manufacturer: Dr. Harold Katz, LLC
Category: otc | Type: HUMAN OTC DRUG LABEL
Date: 20210210

ACTIVE INGREDIENTS: SODIUM FLUORIDE 0.0024 g/1 g
INACTIVE INGREDIENTS: WATER; SORBITOL; XYLITOL; HYDRATED SILICA; GLYCERIN; SODIUM LAUROYL SARCOSINATE; POTASSIUM PYROPHOSPHATE; ZINC GLUCONATE; SODIUM PYROPHOSPHATE; SODIUM CHLORITE; MENTHA PIPERITA; ALOE VERA LEAF; SODIUM BENZOATE; UBIDECARENONE

PerioTherapy Healthy Gums

Active Ingredient

Sodium fluoride 0.24%

(0.14% W/V fluoride ion)

Purpose

Anticavity Fluoride Dentrifice

Uses

Aids in the prevention of dental cavities

Warnings

If more than used for brushing is accidentally
swallowed, get medical help or contact a Poison Control Center right away.

Warnings

Keep out of reach of children under 6 years of age.

Other information

- If spilled on fabrics, wash out immediately.
- This product was sealed with protective packaging at

the laboratory.
• If seal is missing, do not use.

Inactive Ingredients

Water (Aqua), Hydrated Silica, Sorbitol, Glycerin, Tetrapotassium Pyrophosphate, Tetrasodium Pyrophosphate, Xylitol, Sodium Lauroyl Sarcosinate, Sodium Chlorite (PeriO2), Mentha Piperita (Peppermint) Oil, Zinc Gluconate (ZincRx), Aloe Barbadensis Leaf Juice, Sodium Benzoate, Ubiquinone.